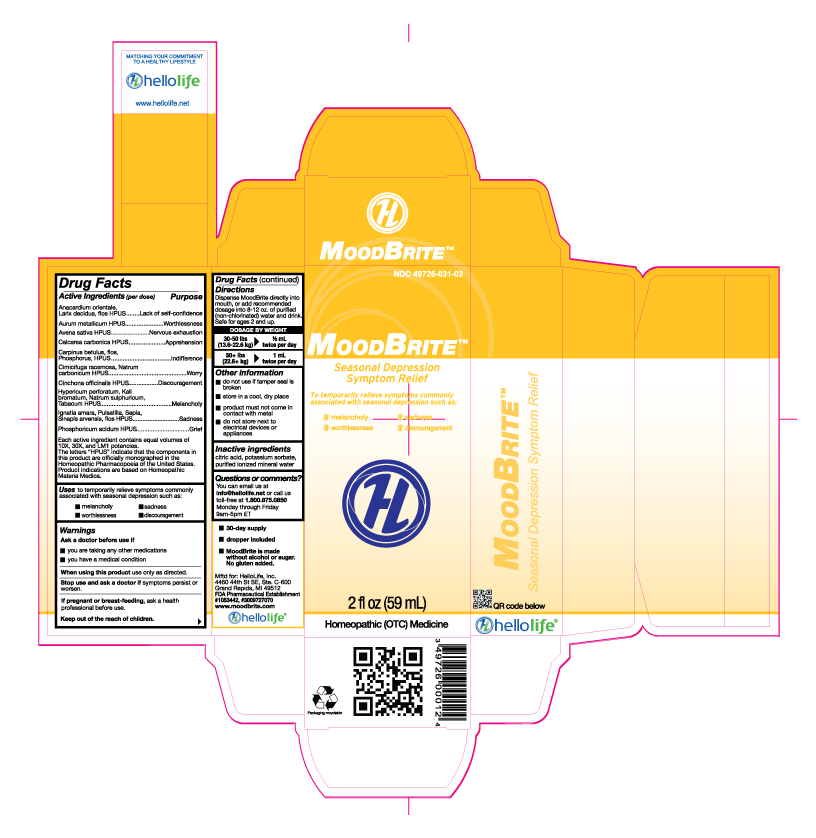 DRUG LABEL: MoodBrite
NDC: 49726-031 | Form: LIQUID
Manufacturer: Hello Life, Inc.
Category: homeopathic | Type: HUMAN OTC DRUG LABEL
Date: 20181226

ACTIVE INGREDIENTS: SEMECARPUS ANACARDIUM JUICE 10 [hp_X]/59 mL; LARIX DECIDUA FLOWERING TOP 10 [hp_X]/59 mL; GOLD 10 [hp_X]/59 mL; AVENA SATIVA FLOWERING TOP 10 [hp_X]/59 mL; OYSTER SHELL CALCIUM CARBONATE, CRUDE 10 [hp_X]/59 mL; CINCHONA OFFICINALIS BARK 10 [hp_X]/59 mL; HYPERICUM PERFORATUM 10 [hp_X]/59 mL; POTASSIUM BROMIDE 10 [hp_X]/59 mL; SODIUM SULFATE 10 [hp_X]/59 mL; TOBACCO LEAF 10 [hp_X]/59 mL; STRYCHNOS IGNATII SEED 10 [hp_X]/59 mL; PULSATILLA VULGARIS 10 [hp_X]/59 mL; SEPIA OFFICINALIS JUICE 10 [hp_X]/59 mL; SINAPIS ARVENSIS FLOWERING/FRUITING TOP 10 [hp_X]/59 mL; SODIUM CARBONATE 10 [hp_X]/59 mL; PHOSPHORIC ACID 10 [hp_X]/59 mL; PHOSPHORUS 10 [hp_X]/59 mL; CARPINUS BETULUS FLOWERING TOP 10 [hp_X]/59 mL; BLACK COHOSH 10 [hp_X]/59 mL
INACTIVE INGREDIENTS: ANHYDROUS CITRIC ACID; POTASSIUM SORBATE; WATER

Active Ingredients (per dose)

Anacardium orientale, Larix decidua, flos HPUS

Aurum metallicum HPUS

Avena sativa HPUS

Calcarea carbonica HPUS

Carpinus betulus, flos, Phosphorus, HPUS

Cimicifuga racemosa, Natrum carbonicum HPUS
Cinchona officinalis HPUS

Hypericum perforatum, Kali bromatum, Natrum sulphuricum, Tabacum HPUS

Ignatia amara, Pulsatilla, Sepia, Sinapis arvensis, flos HPUS

Phosphoricum acidum HPUS
Each active ingredient contains equal volumes of 10X, 30X and LM1 potencies. The letters "HPUS" indicate that the components in this product are officially monographed in the Homeopathic Pharmacopoeia of the United States. Product indications are based on Homeopathic Materia Medica.

Purpose

Anacardium orientale, Larix decidua, flos HPUS.............................................................................................Lack of self-confidence

Aurum metallicum HPUS..................................................................................................................................Worthlessness

Avena sativa HPUS........................................................................................................................................ Nervous exhaustion

Calcarea carbonica HPUS..............................................................................................................................Apprehension

Carpinus betulus, flos, Phosphorus, HPUS....................................................................................................Indifference
Cimicifuga racemosa, Natrum carbonicum HPUS............................................................................................Worry

Cinchona officinalis HPUS...............................................................................................................................Discouragement

Hypericum perforatum, Kali bromatum, Natrum sulphuricum, Tabacum HPUS...............................................Melancholy

Ignatia amara, Pulsatilla, Sepia, Sinapis arvensis, flos HPUS.........................................................................Sadness

Phosphoricum acidum HPUS...........................................................................................................................Grief

Uses

to temporarily relieve symptoms commonly associated with seasonal depression such as:

- melancholy
- sadness
- worthlessness
- discouragement

Warnings

Ask a doctor before use if
• you are taking any other medications
• you have a medical condition

When using this product use only as directed.

Stop use and ask a doctor if symptoms persist or worsen.

PREGNANCY OR BREAST FEEDING

If pregnant or breast-feeding, ask a health professional before use.

Keep out of the reach of children.

Directions

Dispense MoodBrite directly into mouth, or add recommended dosage into 8-12 oz. purified (non-chlorinated) water and drink. Safe for ages 2 and up.
DOSAGE BY WEIGHT
30-50 lbs 1/2 mL
(13.6-22.6 kg) twice per day
50+ lbs 1 mL
(22.6+ kg) twice per day

Other information

- do not use if tamper seal is broken
- store in a cool, dry place
- product must not come in contact with metal
- do not store next to electrical devices or appliances

Inactive ingredients

citric acid, potassium sorbate, purified ionized mineral water

Questions or comments?

You can email us at info@hellolife.net or call us toll-free at 1.800.875.0850
Monday through Friday 9am-5pm ET

DESCRIPTION

• 30-day supply
• dropper included
• MoodBrite is made without alcohol or sugar. No gluten added.
Mftd for: HelloLife, LLC.
4460 44th St SE, Ste. C-600
Grand Rapids, MI 49512
FDA Pharmaceutical Establishment
#1053442, #3009727070
www.moodbrite.com

PACKAGE LABEL

NDC 49726-031-02

MOODBRITETM

Seasonal Depression Symptom Relief
To temporarily relieve symptoms commonly associated with seasonal depression such as:

• melancholy
• sadness
• worthlessness
• discouragement

2 fl oz (59 mL)

Homeopathic (OTC) Medicine